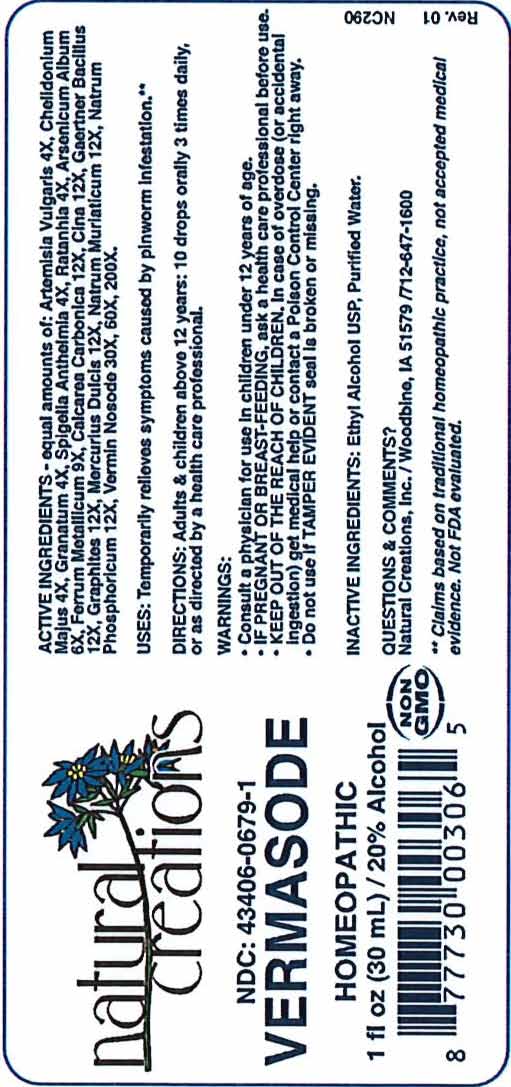 DRUG LABEL: Vermasode
NDC: 43406-0679 | Form: LIQUID
Manufacturer: Natural Creations, Inc
Category: homeopathic | Type: HUMAN OTC DRUG LABEL
Date: 20251218

ACTIVE INGREDIENTS: ARTEMISIA VULGARIS ROOT 4 [hp_X]/1 mL; CHELIDONIUM MAJUS WHOLE 4 [hp_X]/1 mL; PUNICA GRANATUM ROOT BARK 4 [hp_X]/1 mL; SPIGELIA ANTHELMIA WHOLE 4 [hp_X]/1 mL; KRAMERIA LAPPACEA ROOT 4 [hp_X]/1 mL; ARSENIC TRIOXIDE 6 [hp_X]/1 mL; IRON 9 [hp_X]/1 mL; OYSTER SHELL CALCIUM CARBONATE, CRUDE 12 [hp_X]/1 mL; ARTEMISIA CINA PRE-FLOWERING TOP 12 [hp_X]/1 mL; SALMONELLA ENTERICA ENTERICA SEROVAR ENTERITIDIS 12 [hp_X]/1 mL; GRAPHITE 12 [hp_X]/1 mL; CALOMEL 12 [hp_X]/1 mL; SODIUM CHLORIDE 12 [hp_X]/1 mL; SODIUM PHOSPHATE, DIBASIC, HEPTAHYDRATE 12 [hp_X]/1 mL
INACTIVE INGREDIENTS: ALCOHOL; WATER

Vermasode

ACTIVE INGREDIENT

ACTIVE INGREDIENTS - equal amounts of: Artemisia Vulgaris 4X, Chelidonium Majus 4X, Granatum 4X, Spigelia Anthelmia 4X, Ratanhia 4X, Arsenicum Album 6X, Ferrum Metallicum 9X, Calcarea Carbonica 12X, Cina 12X, Gaertner Bacillus 12X, Graphites 12X, Mercurius Dulcis 12X, Natrum Muriaticum 12X, Natrum Phosphoricum 12X, Vermin Nosode 30X, 60X, 200X

INDICATIONS AND USAGE

USES: Temporarily relieves symptoms caused by pinworm infestation.**

PURPOSE

USES: Temporarily relieves symptoms caused by pinworm infestation.**

DOSAGE AND ADMINISTRATION

DIRECTIONS: Adults & children above 12 years: 10 drops orally 3 times daily, or as directed by a health care professional.

KEEP OUT OF REACH OF CHILDREN

KEEP OUT OF THE REACH OF CHILDREN. In case of overdose (or accidental ingestion) get medical help or contact a Poison Control Center right away.

WARNINGS:

- Consult a physician for use in children under 12 years of age.
- IF PREGNANT OR BREAST-FEEDING, ask a health care professional before use.
- KEEP OUT OF THE REACH OF CHILDREN. In case of overdose (or accidental ingestion) get medical help or contact a Poison Control Center right away.
- Do not use if TAMPER EVIDENT seal is broken or missing.

INACTIVE INGREDIENTS: Ethyl Alcohol USP, Purified Water.

QUESTIONS & COMMENTS?

Natural Creations, Inc. / Woodbine, IA 51579 / 712-647-1600

REFERENCES

**Claims based on traditional homeopathic practice, not accepted medical evidence. Not FDA evaluated.

PACKAGE LABEL

NDC:43406-0679-1

Vermasode

HOMEOPATHIC

1 fl oz (30mL) / 20% Alcohol